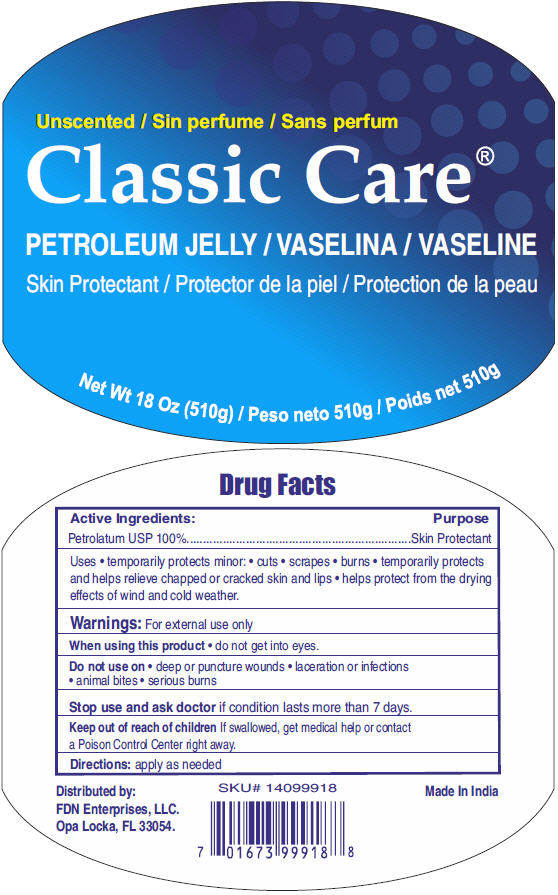 DRUG LABEL: Classic Care 
NDC: 60691-126 | Form: JELLY
Manufacturer: FDN Enterprises, LLC
Category: otc | Type: HUMAN OTC DRUG LABEL
Date: 20150508

ACTIVE INGREDIENTS: Petrolatum 100 g/100 g

Classic Care®
Petroleum Jelly

Drug Facts

Active Ingredients

Petrolatum USP 100%

Purpose

Skin Protectant

Uses

- temporarily protects minor:
  - cuts
  - scrapes
  - burns
- temporarily protects and helps relieve chapped or cracked skin and lips
- helps protect from the drying effects of wind and cold weather.

Warnings

For external use only

When using this product

- do not get into eyes.

Do not use on

- deep or puncture wounds
- laceration or infections
- animal bites
- serious burns

Stop use and ask doctor if condition lasts more than 7 days.

Keep out of reach of children If swallowed, get medical help or contact a Poison Control Center right away.

Directions

apply as needed

Distributed by:
FDN Enterprises, LLC.
Opa Locka, FL 33054.

PRINCIPAL DISPLAY PANEL - 510 g Jar Label

Unscented

Classic Care®

PETROLEUM JELLY

Skin Protectant

Net Wt 18 Oz (510g)